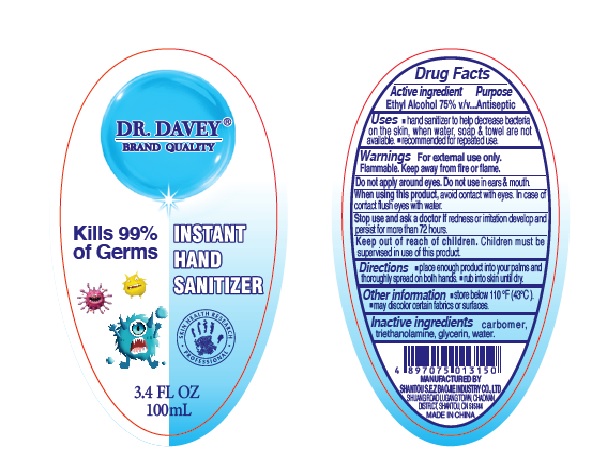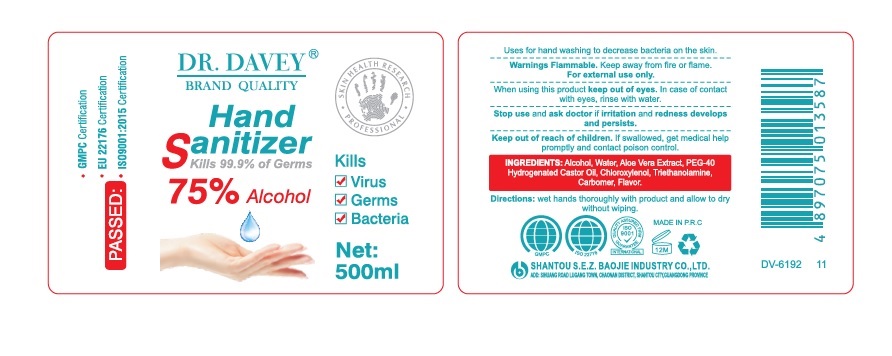 DRUG LABEL: DR.DAVEY
NDC: 74913-001 | Form: LIQUID
Manufacturer: SHANTOU S.E.Z BAOJIE INDUSTRY CO., LTD
Category: otc | Type: HUMAN OTC DRUG LABEL
Date: 20200424

ACTIVE INGREDIENTS: ALCOHOL 75 mL/100 mL
INACTIVE INGREDIENTS: CARBOMER HOMOPOLYMER, UNSPECIFIED TYPE; TROLAMINE; GLYCERIN; WATER

Active lngredient

Ethyl Alcohol

Purpose

Antiseptic

Uses

• hand sanitizer to help decrease bacteria on the skin, when water, soap & towel are not available.
• recommended for repeated use.

Warnings

For external use only.

Flammable. Keep away from fire or flame.

Do not apply around eyes. Do not use in ears & mouth.

When using this product, avoid contact with eyes. In case of contact flush eyes with water.

Stop use and ask a doctor if redness or irritation develop and persist for more than 72 hours.

Keep out of reach of children.

Children must be supervised in use of this product.

Directions

• place enough product into your palms and thoroughly spread on both hands.
• rub into skin until dry.

Keep out of reach of children

Children must be supervised in use of this product.

Other information

• store below 110℉ (43℃).
• may discolor certain fabrics or surfaces.

Inactive ingredient

carbomer, triethanolamine, glycerin, water.